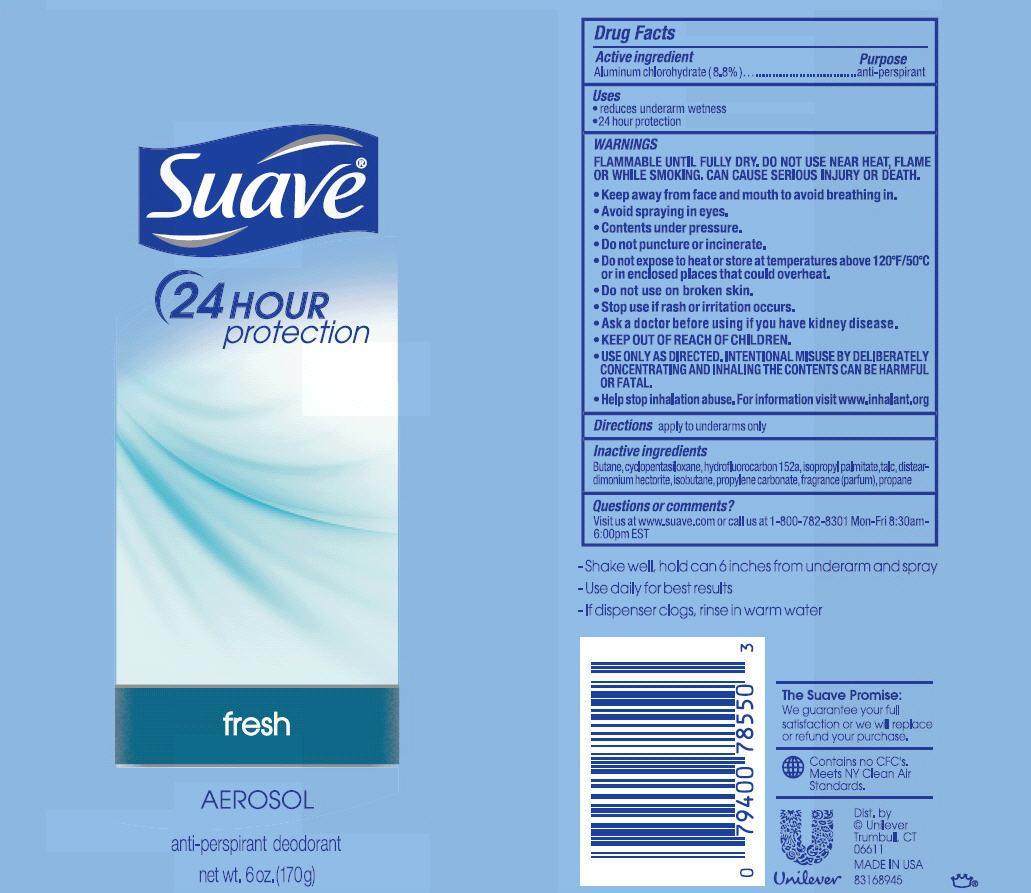 DRUG LABEL: Suave
NDC: 64942-1293 | Form: AEROSOL, SPRAY
Manufacturer: Conopco Inc. d/b/a Unilever
Category: otc | Type: HUMAN OTC DRUG LABEL
Date: 20211201

ACTIVE INGREDIENTS: ALUMINUM CHLOROHYDRATE 8.8 g/100 g
INACTIVE INGREDIENTS: BUTANE; 1,1-DIFLUOROETHANE; CYCLOMETHICONE 5; ISOPROPYL PALMITATE; TALC; DISTEARDIMONIUM HECTORITE; ISOBUTANE; PROPYLENE CARBONATE; PROPANE

Suave Aerosol Fresh Antiperspirant Deodorant

Active ingredient

Aluminum chlorohydrate (8.8%)

Purpose

anti-perspirant

Uses
· reduces underarm wetness
· 24 hour protection

WARNINGS
FLAMMABLE UNTIL FULLY DRY. DO NOT USE NEAR HEAT, FLAME OR WHILE SMOKING. CAN CAUSE SERIOUS INJURY OR DEATH.
• Keep away from face and mouth to avoid breathing in.
• Avoid spraying in eyes.
• Contents under pressure.
• Do not puncture or incinerate.
• Do not expose to heat or store at temperatures above 120 degrees F/50 degrees C or in enclosed places that could overheat.
• USE ONLY AS DIRECTED. INTENTIONAL MISUSE BY DELIBERATELY CONCENTRATING AND INHALING THE CONTENTS CAN BE HARMFUL OR FATAL.
• Help stop inhalation abuse. For information visit www.inhalant.org

• Do not use on broken skin.

• Stop use if rash or irritation occurs.

• Ask a doctor before using if you have kidney disease.

• KEEP OUT OF REACH OF CHILDREN.

Directions

apply to underarms only

Inactive ingredients

Butane, cyclopentasiloxane, hydrofluorcarbon 152a, isopropyl palmitate, talc, disteardimonium hectorite, isobutane, fragrance (parfum), propylene carbonate, propane

Questions or comments?
Visit us at www.suave.com or call us at 1-800-782-8301 Mon-Fri 8:30 am - 6:00 pm EST